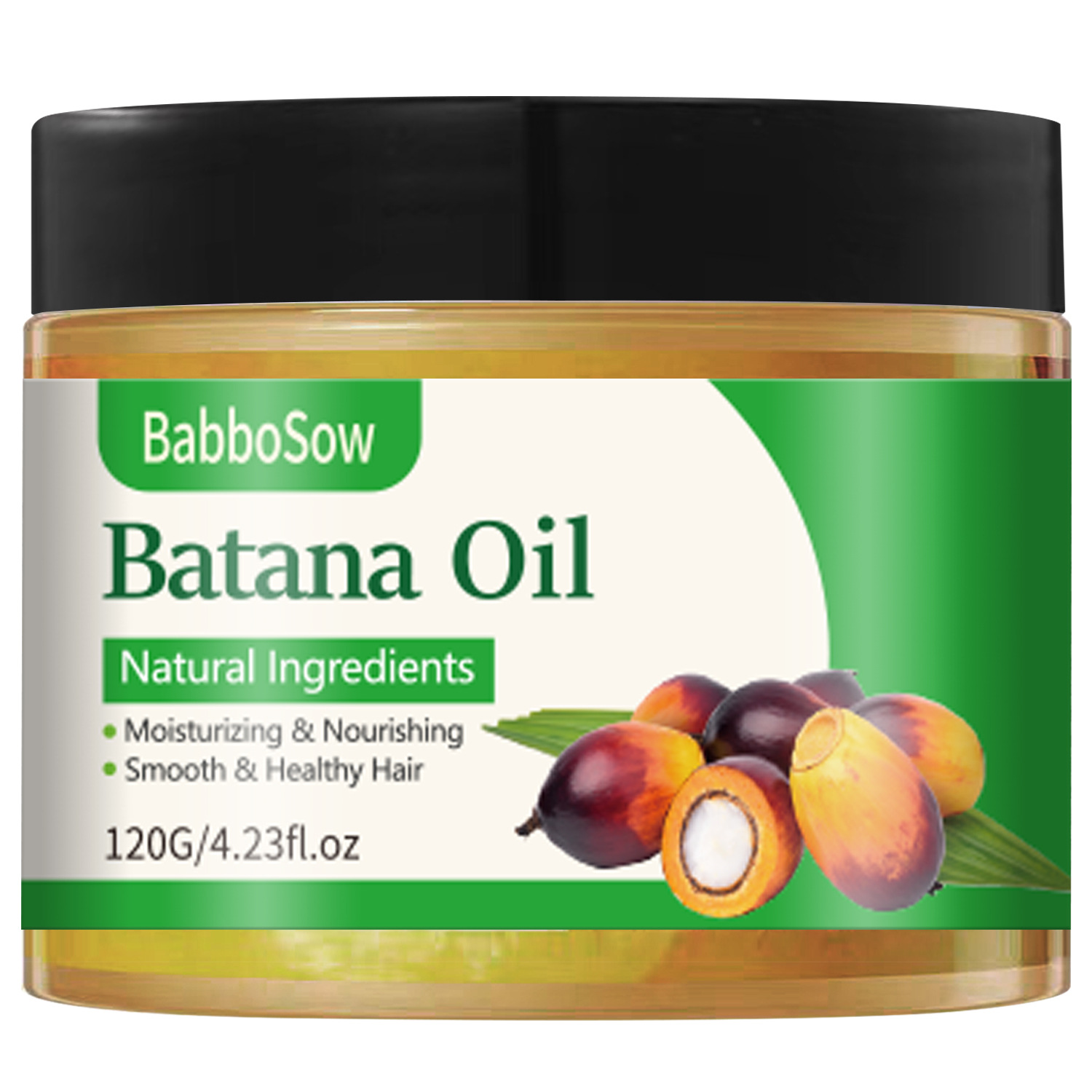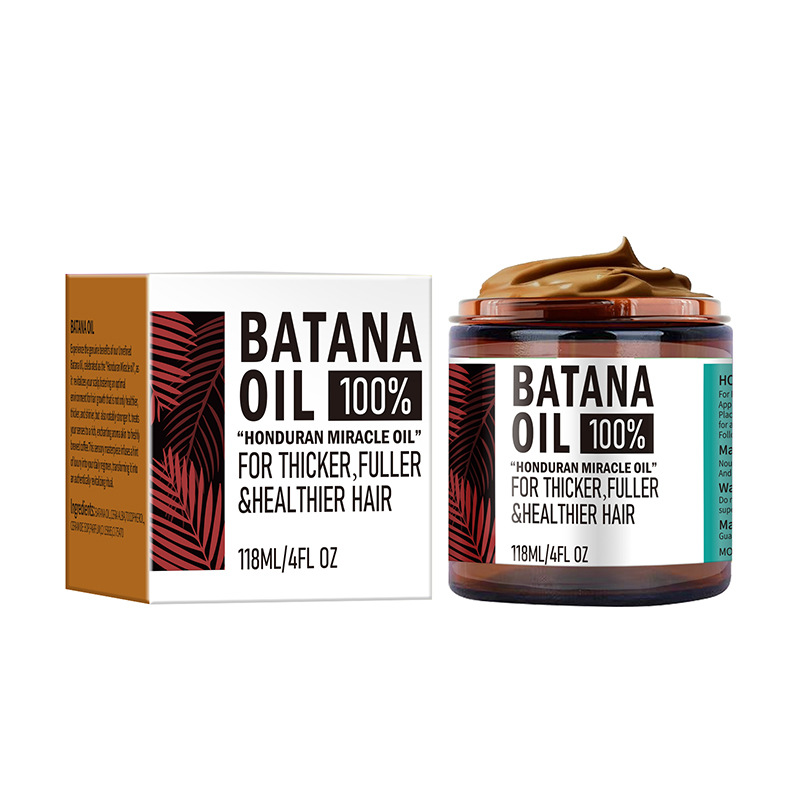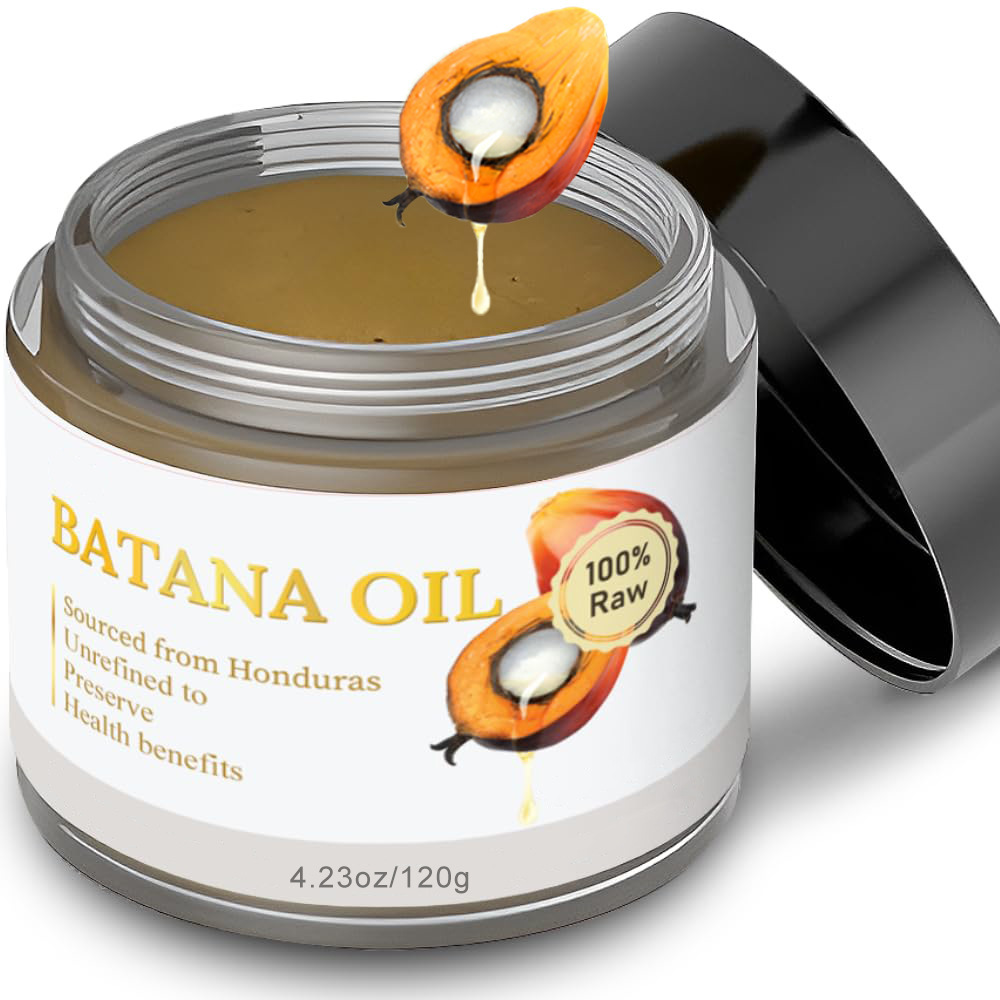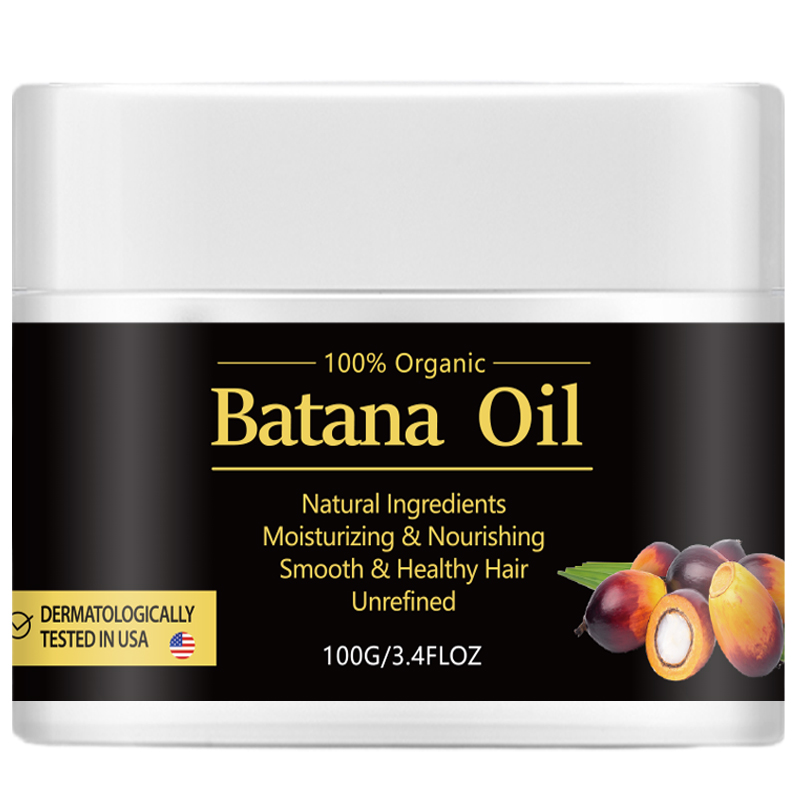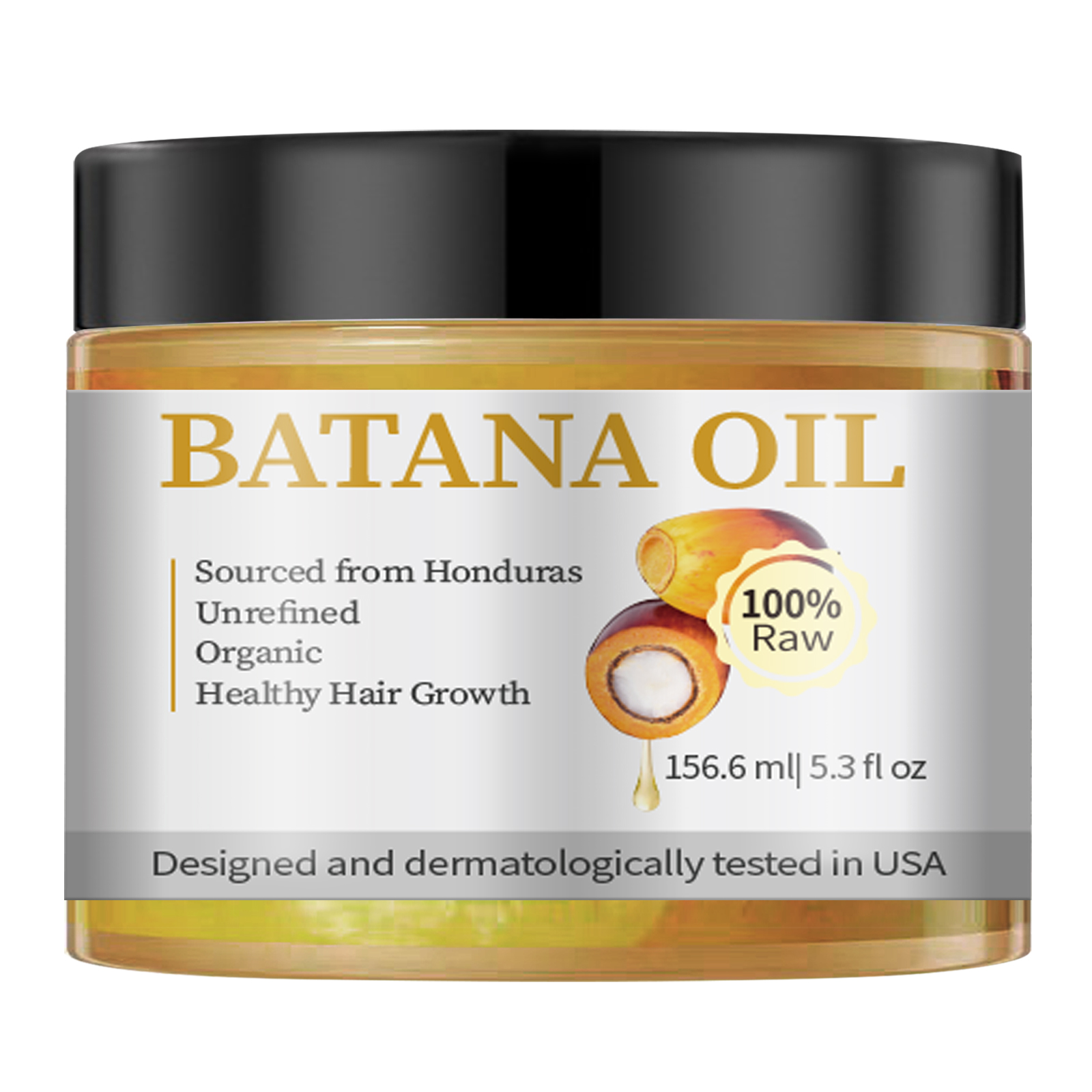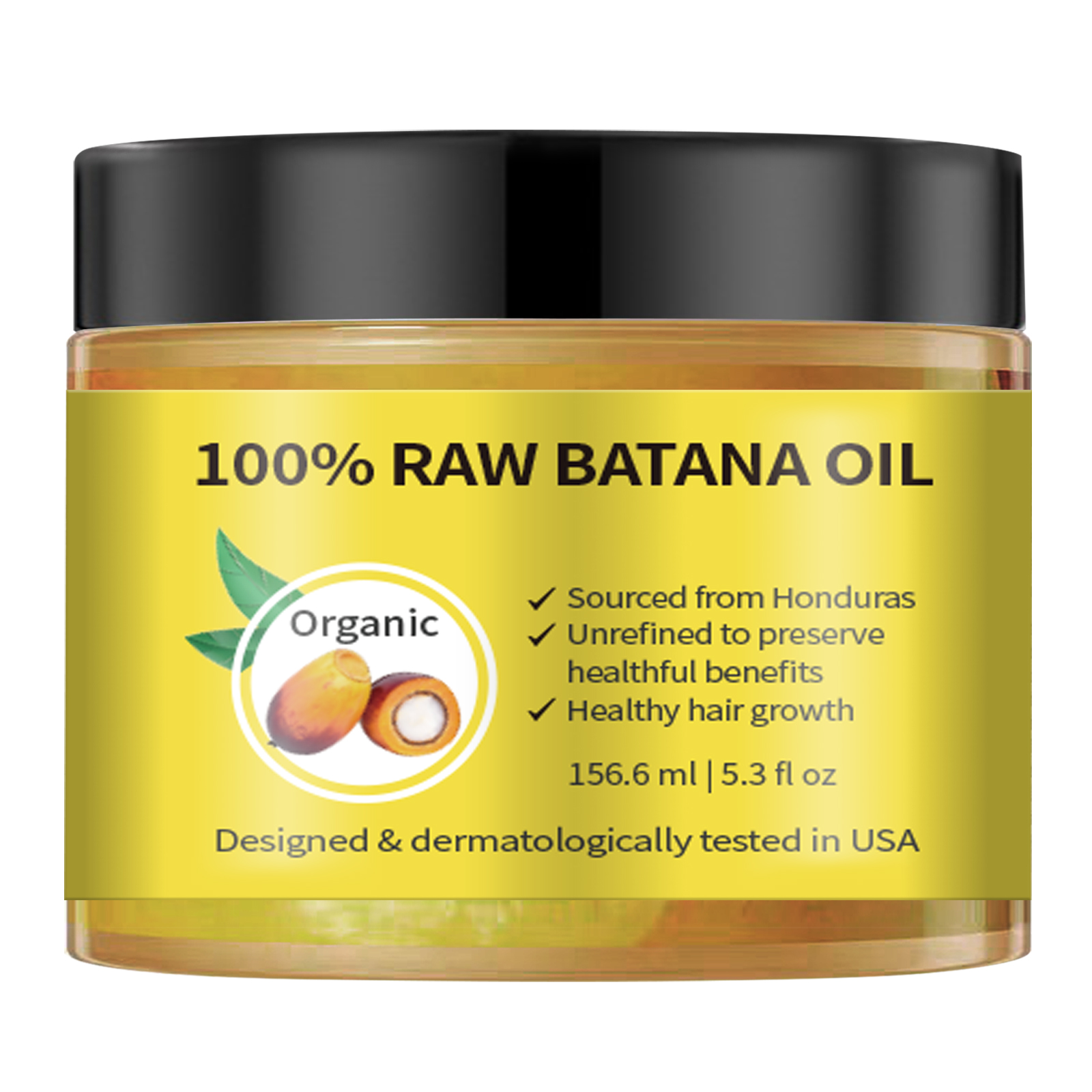 DRUG LABEL: SY Batana Hair Oil
NDC: 84778-030 | Form: CREAM
Manufacturer: Guangzhou Yixin Cross-border E-commerce Co., Ltd.
Category: otc | Type: HUMAN OTC DRUG LABEL
Date: 20241107

ACTIVE INGREDIENTS: ELAEIS OLEIFERA SEED OIL 100 g/100 mL
INACTIVE INGREDIENTS: WATER

COMPONENTS

Elaeis Oleifera Kernel Oil 100g

PURPOSE

Hair care solutions for thicker, stronger, smoother and more hydrating hair

INDICATIONS AND USAGE

Open the outer packaging box and open the plastic bottle cap

WARNINGS

It is recommended to conduct an allergy test on a small piece of skin before use. If redness, swelling, itching of the epidermis or other reactions occur, please stop using it.

DOSAGE AND ADMINISTRATION

For external use only.

Do not use on wounds, inflamed or infected skin.

WHEN USING

This product is for external use only. Please avoid contact with eyes. If it gets into eyes accidentally, rinse immediately with clean water.

STOP USE

It is recommended to conduct an allergy test on a small skin before use. If redness, swelling, epidermal itching or other reactions occur, please stop using it.
Do not use on wounds, inflammation or infected skin.

Keep out of reach of children and pets.

Do not use this box incribs,beds,carriages or play pens,This Product is not a TOY.

INACTIVE INGREDIENT

Water